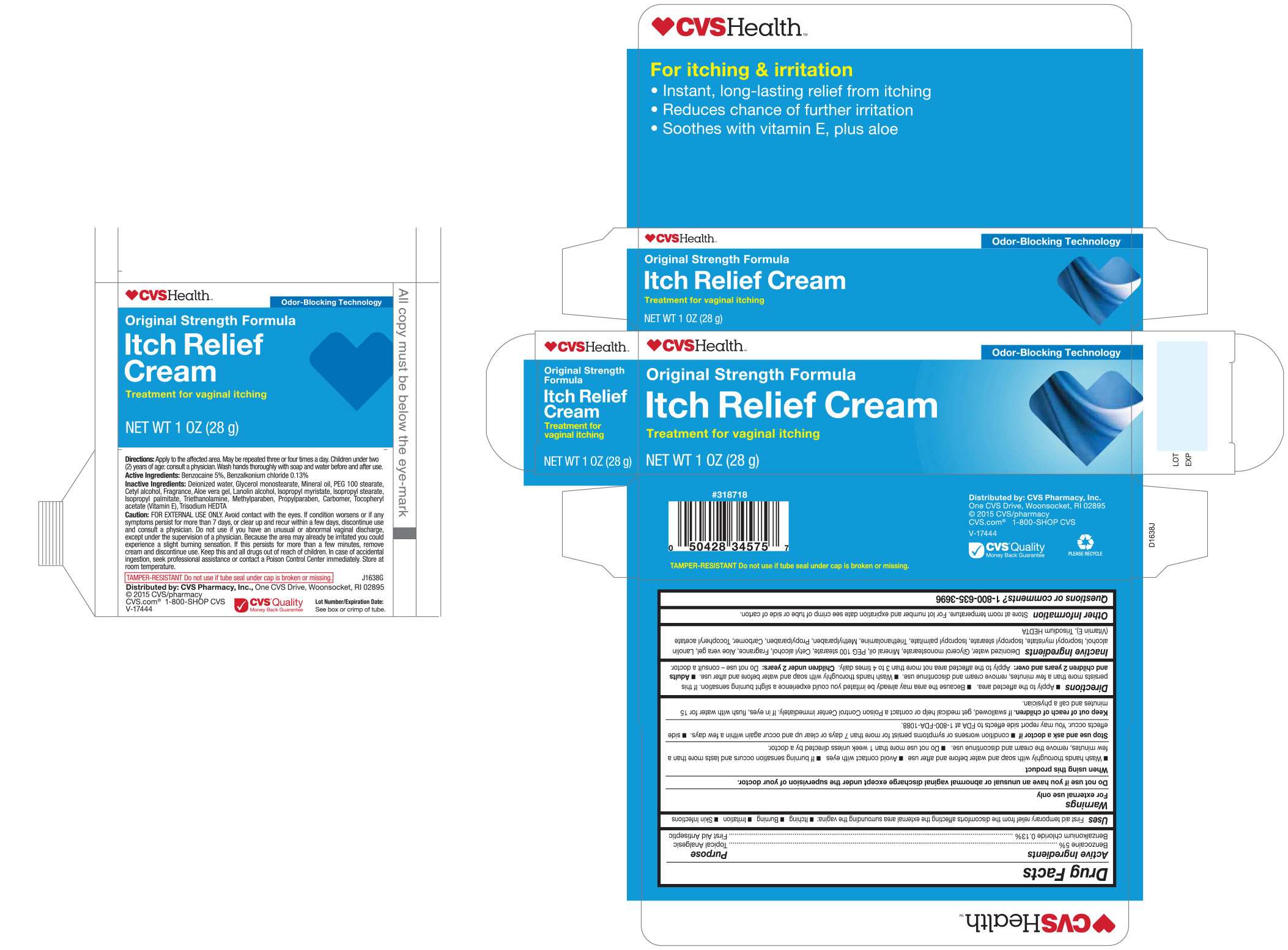 DRUG LABEL: CVS Pharmacy
NDC: 69842-638 | Form: CREAM
Manufacturer: CVS Pharmacy
Category: otc | Type: HUMAN OTC DRUG LABEL
Date: 20170104

ACTIVE INGREDIENTS: BENZOCAINE 0.05 g/1 g; BENZALKONIUM CHLORIDE 0.0013 g/1 g
INACTIVE INGREDIENTS: ALOE VERA LEAF; CARBOMER HOMOPOLYMER TYPE C (ALLYL PENTAERYTHRITOL CROSSLINKED); CETYL ALCOHOL; WATER; GLYCERYL MONOSTEARATE; ISOPROPYL PALMITATE; ISOPROPYL STEARATE; LANOLIN ALCOHOLS; METHYLPARABEN; MINERAL OIL; PEG-100 STEARATE; PROPYLPARABEN; .ALPHA.-TOCOPHEROL ACETATE; TROLAMINE; TRISODIUM HEDTA; ISOPROPYL MYRISTATE

Drug Facts

Active Ingredients

Benzocaine 5%

Benzalkonium Chloride 0.13%

Purpose

Topical Analgesic

First Aid Antiseptic

Uses

First aid temporary relief from the discomforts affecting the external area surrounding the vagina:

- Itching
- Burning
- Irritation
- Skin infections

Warnings

For external use only.

Do not use if you have unusual or abnormal vaginal discharge except under the supervision of your doctor.

When using this product

- Wash hand thoroughly with soap and water before and after use
- Avoid contact with eyes.
- If burning sensation occurs and lasts more than a few minutes remove the cream and discontinue use.
- Do not use more than 1 week unless directed by a doctor

Stop use and ask a doctor if

- condition worsens or symptoms persist for more than 7 days or clear up and occur again within a few days.
- side effect occur. You may report sude effect to FDA at 1-800-FDA-1088

Keep out of reach of children

If swallowed, get medical help or contact a Poison Control Center immediately. If in eyes, flush with water for 15 minutes and call a physician.

WHEN USING

- Apply to the affected area.
- Because the area may already be irritated you could experience a slight burning sensation. If this persists more than a few minutes, remove cream and discontinue use.
- Wash hand thoroughly with soap and water before and after use.

OTHER SAFETY INFORMATION

Store at room temperature. For lot number and expiration dates see crimp of tube or side of box.

INACTIVE INGREDIENT

Deionized Water, Glycerol Monostearate, Mineral Oil, PEG 100 Stearate, Cetyl Alcohol, Fragrance, Aloe Vera Gel, Lanolin Alcohol, Isopropyl Myristate, Isopropyl Stearate, Isopropyl Palmitate, Triethanolamine, Methylparaben, Propylparaben, Carbomer, Tocopheryl Acetate (Vitamin E), Trisodium HEDTA.

Questions or Comments

1-800-635-3696

DOSAGE AND ADMINISTRATION

- Adults and children 2 years and over: Apply to the affected area not more than 3 to 4 times daily.
- Children under 2 years: Do not use-consult a doctor.